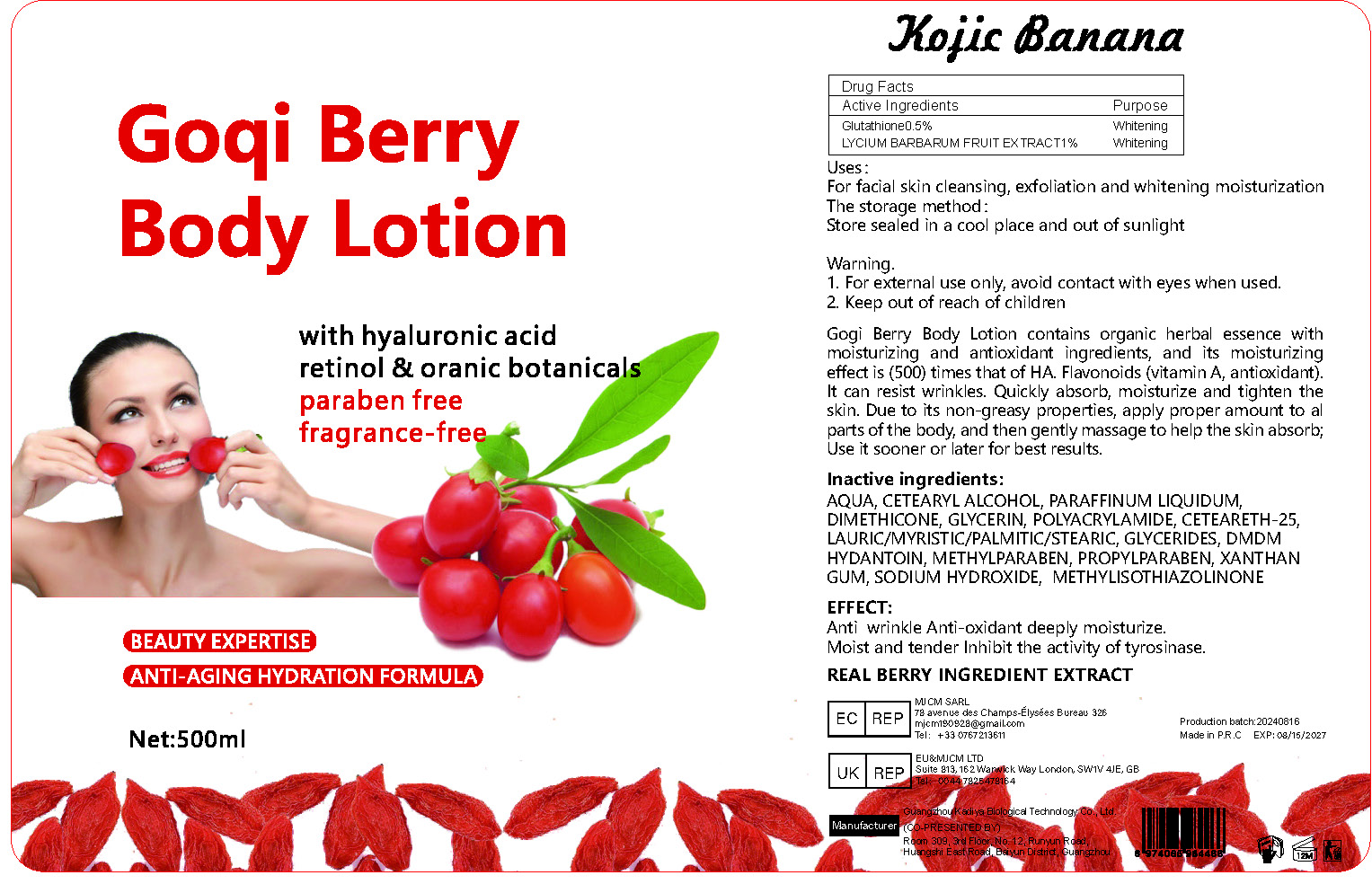 DRUG LABEL: Goqi Berry Body Lotio
NDC: 84423-039 | Form: CREAM, AUGMENTED
Manufacturer: Guangzhou Kadiya Biotechnology Co., Ltd.
Category: otc | Type: HUMAN OTC DRUG LABEL
Date: 20240827

ACTIVE INGREDIENTS: LYCIUM BARBARUM FRUIT 5 mg/500 mL; GLUTATHIONE 2.5 mg/500 mL
INACTIVE INGREDIENTS: SODIUM HYDROXIDE; CETEARETH-25; METHYLPARABEN; PROPYLPARABEN; METHYLISOTHIAZOLINONE; GLYCERIN; DMDM HYDANTOIN; MINERAL OIL; XANTHAN GUM; DIMETHICONE; POLYACRYLAMIDE (10000 MW); CETOSTEARYL ALCOHOL

PURPOSE

For facial skin cleansing, exfoliation and whitening moisturization

INACTIVE INGREDIENT

AQUA、CETEARYL ALCOHOL、PARAFFINUM LIQUIDUM、DIMETHICONE、GLYCERIN、POLYACRYLAMIDE、CETEARETH-25、LAURIC/MYRISTIC/PALMITIC/STEARIC、GLYCERIDES、DMDM HYDANTOIN、METHYLPARABEN、PROPYLPARABEN、XANTHAN GUM、SODIUM HYDROXIDE、 METHYLISOTHIAZOLINONE

WARNINGS

1、For external use only, avoid contact with eyes when used
2、Keep out of reach of children

INDICATIONS AND USAGE

Gogi Berry Body Lotion contains organic herbal essence with moisturizing and antioxidant ingredients, and its moisturizing effect is (500) times that of HA. Flavonoids (vitamin A, antioxidant). It can resist wrinkles. Quickly absorb, moisturize and tighten the skin. Due to its non-greasy properties, apply proper amount to al parts of the body, and then gently massage to help the skin absorb; Use it sooner or later for best results.

DOSAGE AND ADMINISTRATION

Gogi Berry Body Lotion contains organic herbal essence with moisturizing and antioxidant ingredients, and its moisturizing effect is (500) times that of HA. Flavonoids (vitamin A, antioxidant). It can resist wrinkles. Quickly absorb, moisturize and tighten the skin. Due to its non-greasy properties, apply proper amount to al parts of the body, and then gently massage to help the skin absorb; Use it sooner or later for best results.

Active Ingredients
Glutathione0.5%
LYCIUM BARBARUM FRUIT EXTRACT1%

KEEP OUT OF REACH OF CHILDREN SECTION

PACKAGE LABEL

Active Ingredients
Glutathione0.5%
LYCIUM BARBARUM FRUIT EXTRACT1%

Uses：
For facial skin cleansing, exfoliation and whitening moisturization
The storage method：
Store sealed in a cool place and out of sunlight

Warning.
1、For external use only, avoid contact with eyes when used
2、Keep out of reach of children

Inactive ingredients：
AQUA、CETEARYL ALCOHOL、PARAFFINUM LIQUIDUM、DIMETHICONE、GLYCERIN、POLYACRYLAMIDE、CETEARETH-25、LAURIC/MYRISTIC/PALMITIC/STEARIC、GLYCERIDES、DMDM HYDANTOIN、METHYLPARABEN、PROPYLPARABEN、XANTHAN GUM、SODIUM HYDROXIDE、 METHYLISOTHIAZOLINONE